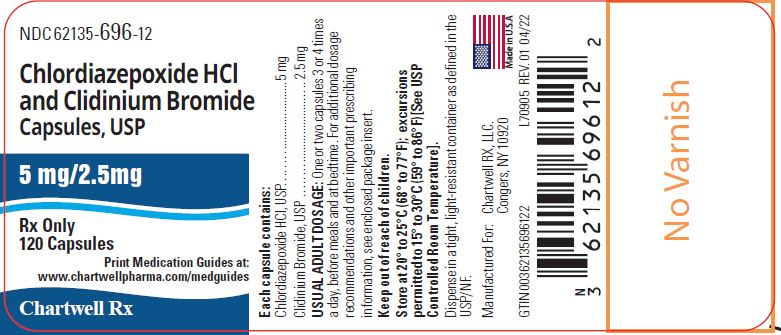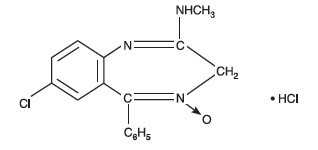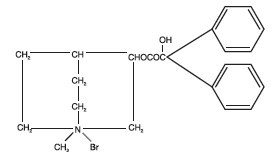 DRUG LABEL: CHLORDIAZEPOXIDE HYDROCHLORIDE AND CLIDINIUM BROMIDE
NDC: 62135-696 | Form: CAPSULE
Manufacturer: Chartwell RX, LLC
Category: prescription | Type: HUMAN PRESCRIPTION DRUG LABEL
Date: 20251210
DEA Schedule: CIV

ACTIVE INGREDIENTS: CHLORDIAZEPOXIDE HYDROCHLORIDE 5 mg/1 1; CLIDINIUM BROMIDE 2.5 mg/1 1
INACTIVE INGREDIENTS: LACTOSE MONOHYDRATE; STARCH, CORN; TALC; TITANIUM DIOXIDE; D&C YELLOW NO. 10; FD&C GREEN NO. 3; GELATIN; AMMONIA; FERROSOFERRIC OXIDE; POTASSIUM HYDROXIDE; PROPYLENE GLYCOL; SHELLAC

Chlordiazepoxide Hydrochloride and Clidinium Bromide Capsules USP, 5 mg/2.5 mg

WARNING: RISKS FROM CONCOMITANT USE WITH OPIOIDS

Concomitant use of benzodiazepines and opioids may result in profound sedation, respiratory depression, coma, and death (see WARNINGS and PRECAUTIONS).

- Reserve concomitant prescribing of these drugs for use in patients for whom alternative treatment options are inadequate.
- Limit dosages and durations to the minimum required.
- Follow patients for signs and symptoms of respiratory depression and sedation.

DESCRIPTION

Chlordiazepoxide hydrochloride and clidinium bromide capsules USP, 5 mg/2.5 mg combines in a single capsule formulation the antianxiety action of chlordiazepoxide hydrochloride and the anticholinergic/spasmolytic effects of clidinium bromide.

Each chlordiazepoxide hydrochloride and clidinium bromide capsules USP, 5 mg/2.5 mg contains the active ingredients 5 mg chlordiazepoxide hydrochloride and 2.5 mg clidinium bromide. Each capsule also contains the inactive ingredients corn starch, lactose monohydrate, talc, sodium lauryl sulfate, D&C Yellow No. 10, FD&C Green No. 3, titanium dioxide, and gelatin. The imprinting ink contains ammonia solution, black iron oxide, potassium hydroxide, propylene glycol, and shellac.

Chlordiazepoxide hydrochloride is a versatile, therapeutic agent of proven value for the relief of anxiety and tension. It is indicated when anxiety, tension or apprehension are significant components of the clinical profile. It is among the safer of the effective psychopharmacologic compounds.

Chlordiazepoxide hydrochloride is 7-chloro-2-(methylamino)-5-phenyl-3H-1,4-benzodiazepine 2-oxide monohydrochloride. A white to slightly yellow, crystalline powder, it is soluble in water. It is unstable in solution and the powder must be protected from light. The molecular weight is 336.2. The structural formula of chlordiazepoxide hydrochloride is as follows:

Clidinium bromide is a synthetic anticholinergic agent which has been shown in experimental and clinical studies to have a pronounced antispasmodic and antisecretory effect on the gastrointestinal tract. Structurally clidinium bromide is:

ANIMAL PHARMACOLOGY

Chlordiazepoxide hydrochloride has been studied extensively in many species of animals and these studies are suggestive of action on the limbic system of the brain, which recent evidence indicates is involved in emotional responses. Hostile monkeys were made tame by oral drug doses, which did not cause sedation. Chlordiazepoxide hydrochloride revealed a "taming-action with the elimination of fear and aggression". The taming effect of chlordiazepoxide hydrochloride was further demonstrated in rats made vicious by lesions in the septal area of the brain. The drug dosage which effectively blocked the vicious reaction was well below the dose which caused sedation in these animals.

The oral LD50 of single doses of chlordiazepoxide hydrochloride, calculated according to the method of Miller and Tainter, is 720 ± 51 mg/kg as determined in mice observed over a period of 5 days following dosage.

Clidinium bromide is an effective anticholinergic agent with activity approximating that of atropine sulfate against acetylcholine-induced spasms in isolated intestinal strips. On oral administration in mice, it proved an effective antisialagogue in preventing pilocarpine-induced salivation. Spontaneous intestinal motility in both rats and dogs is reduced following oral dosing with 0.1 to 0.25 mg/kg. Potent cholinergic ganglionic blocking effects (vagal) were produced with intravenous usage in anesthetized dogs.

Oral doses of 2.5 mg/kg to dogs produced signs of nasal dryness and slight pupillary dilation. In two other species, monkeys and rabbits, doses of 5 mg/kg, po, given three times daily for 5 days did not produce apparent secretory or visual changes.

The oral LD50 of single doses of clidinium bromide is 860 ± 57 mg/kg as determined in mice observed over a period of 5 days following dosage; the calculations were made according to the method of Miller and Tainter.

Effects on Reproduction

Reproduction studies in rats fed chlordiazepoxide hydrochloride, 10, 20 and 80 mg/kg daily, and bred through one or two matings showed no congenital anomalies, nor were there adverse effects on lactation of the dams or growth of the newborn. However, in another study at 100 mg/kg daily there was noted a significant decrease in the fertilization rate and a marked decrease in the viability and body weight of offspring which may be attributable to sedative activity, thus resulting in lack of interest in mating and lessened maternal nursing and care of the young. One neonate in each of the first and second matings in the rat reproduction study at the 100 mg/kg dose exhibited major skeletal defects. Further studies are in progress to determine the significance of these findings.

Two series of reproduction experiments with clidinium bromide were carried out in rats, employing dosages of 2.5 and 10 mg/kg daily in each experiment. In the first experiment, clidinium bromide was administered for a 9-week interval prior to mating; no untoward effect on fertilization or gestation was noted. The offspring were taken by caesarean section and did not show a significant incidence of congenital anomalies when compared to control animals. In the second experiment, adult animals were given clidinium bromide for 10 days prior to and through two mating cycles. No significant effects were observed on fertility, gestation, viability of offspring or lactation, as compared to control animals, nor was there a significant incidence of congenital anomalies in the offspring derived from these experiments.

A reproduction study of chlordiazepoxide hydrochloride and clidinium bromide capsules was carried out in rats through two successive matings. Oral daily doses were administered in two concentrations: 2.5 mg/kg chlordiazepoxide hydrochloride with 1.25 mg/kg clidinium bromide or 25 mg/kg chlordiazepoxide hydrochloride with 12.5 mg/kg clidinium bromide. In the first mating, no significant differences were noted between the control or the treated groups, with the exception of a slight decrease in the number of animals surviving during lactation among those receiving the highest dosage. As with all anticholinergic drugs, an inhibiting effect on lactation may occur. In the second mating, similar results were obtained except for a slight decrease in the number of pregnant females and in the percentage of offspring surviving until weaning. No congenital anomalies were observed in both matings in either the control or treated groups. Additional animal reproduction studies are in progress.

INDICATIONS AND USAGE

Chlordiazepoxide hydrochloride and clidinium bromide capsules are indicated to control emotional and somatic factors in gastrointestinal disorders. Chlordiazepoxide hydrochloride and clidinium bromide capsules may also be used as adjunctive therapy in the treatment of peptic ulcer and in the treatment of the irritable bowel syndrome (irritable colon, spastic colon, mucous colitis) and acute enterocolitis.

CONTRAINDICATIONS

Chlordiazepoxide hydrochloride and clidinium bromide capsules are contraindicated in the presence of glaucoma (since the anticholinergic component may produce some degree of mydriasis) and in patients with prostatic hypertrophy and benign bladder neck obstruction. It is contraindicated in patients with known hypersensitivity to chlordiazepoxide hydrochloride and/or clidinium bromide.

WARNINGS

Concomitant use of benzodiazepines, including chlordiazepoxide hydrochloride and clidinium bromide capsules, and opioids may result in profound sedation, respiratory depression, coma, and death. Because of these risks, reserve concomitant prescribing of these drugs for use in patients for whom alternative treatment options are inadequate.

Observational studies have demonstrated that concomitant use of opioid analgesics and benzodiazepines increases the risk of drug-related mortality compared to use of opioids alone. If a decision is made to prescribe chlordiazepoxide hydrochloride and clidinium bromide capsules concomitantly with opioids, prescribe the lowest effective dosages and minimum durations of concomitant use, and follow patients closely for signs and symptoms of respiratory depression and sedation.

Advise both patients and caregivers about the risks of respiratory depression and sedation when chlordiazepoxide hydrochloride and clidinium bromide capsules is used with opioids (see PRECAUTIONS) .

As in the case of other preparations containing CNS-acting drugs, patients receiving chlordiazepoxide hydrochloride and clidinium bromide capsules should be cautioned about possible combined effects with opioids, alcohol and other CNS depressants. For the same reason, they should be cautioned against hazardous occupations requiring complete mental alertness, such as operating machinery or driving a motor vehicle.

Usage In Pregnancy

An increased risk of congenital malformations associated with the use of minor tranquilizers (chlordiazepoxide, diazepam and meprobamate) during the first trimester of pregnancy has been suggested in several studies. Because use of these drugs is rarely a matter of urgency, their use during this period should almost always be avoided. The possibility that a woman of childbearing potential may be pregnant at the time of institution of therapy should be considered. Patients should be advised that if they become pregnant during therapy or intend to become pregnant they should communicate with their physicians about the desirability of discontinuing the drug.

As with all anticholinergic drugs, an inhibiting effect on lactation may occur (see ANIMAL PHARMACOLOGY) .

OVERDOSAGE

Manifestations of chlordiazepoxide hydrochloride overdosage include somnolence, confusion, coma and diminished reflexes. Respiration, pulse and blood pressure should be monitored, as in all cases of drug overdosage, although, in general, these effects have been minimal following chlordiazepoxide hydrochloride overdosage.

While the signs and symptoms of chlordiazepoxide hydrochloride and clidinium bromide capsules overdosage may be produced by either of its components, usually such symptoms will be overshadowed by the anticholinergic actions of clidinium bromide. The symptoms of overdosage of clidinium bromide are excessive dryness of mouth, blurring of vision, urinary hesitancy and constipation.

General supportive measures should be employed, along with immediate gastric lavage. Administer physostigmine 0.5 to 2 mg at a rate of no more than 1 mg per minute. This may be repeated in 1 to 4 mg doses if arrhythmias, convulsions or deep coma recur. Intravenous fluids should be administered and an adequate airway maintained. Hypotension may be combated by the use of levarterenol or metaraminol. Methylphenidate or caffeine and sodium benzoate may be given to combat CNS-depressive effects. Dialysis is of limited value. Should excitation occur, barbiturates should not be used. As with the management of intentional overdosage with any drug, it should be borne in mind that multiple agents may have been ingested.

Withdrawal symptoms of the barbiturate type have occurred after the discontinuation of benzodiazepines (see DRUG ABUSE AND DEPENDENCE).

PRECAUTIONS

In debilitated patients, it is recommended that the dosage be limited to the smallest effective amount to preclude the development of ataxia, oversedation or confusion (not more than 2 Chlordiazepoxide Hydrochloride/Clidinium Bromide capsules per day initially, to be increased gradually as needed and tolerated). In general, the concomitant administration of chlordiazepoxide hydrochloride and clidinium bromide capsules and other psychotropic agents is not recommended. If such combination therapy seems indicated, careful consideration should be given to the pharmacology of the agents to be employed - particularly when the known potentiating compounds such as the MAO inhibitors and phenothiazines are to be used. The usual precautions in treating patients with impaired renal or hepatic function should be observed.

Paradoxical reactions to chlordiazepoxide hydrochloride, e.g., excitement, stimulation and acute rage, have been reported in psychiatric patients and should be watched for during chlordiazepoxide hydrochloride and clidinium bromide capsules therapy. The usual precautions are indicated when chlordiazepoxide hydrochloride is used in the treatment of anxiety states where there is any evidence of impending depression; it should be borne in mind that suicidal tendencies may be present and protective measures may be necessary. Although clinical studies have not established a cause and effect relationship, physicians should be aware that variable effects on blood coagulation have been reported very rarely in patients receiving oral anticoagulants and chlordiazepoxide hydrochloride.

Information for Patients

Inform patients and caregivers that potentially fatal additive effects may occur if chlordiazepoxide hydrochloride and clidinium bromide capsules is used with opioids or other CNS depressants, including alcohol, and not to use these concomitantly unless supervised by a health care provider (see WARNINGS and PRECAUTIONS).

To assure the safe and effective use of benzodiazepines, patients should be informed that, since benzodiazepines may produce psychological and physical dependence, it is advisable that they consult with their physician before either increasing the dose or abruptly discontinuing this drug.

Drug Interactions

The concomitant use of benzodiazepines and opioids increases the risk of respiratory depression because of actions at different receptor sites in the CNS that control respiration. Benzodiazepines interact at GABAA sites and opioids interact primarily at mu receptors. When benzodiazepines and opioids are combined, the potential for benzodiazepines to significantly worsen opioid-related respiratory depression exists. Limit dosage and duration of concomitant use of benzodiazepines and opioids, and follow patients closely for respiratory depression and sedation.

Pediatric Use

Safety and effectiveness in pediatric patients have not been established.

Geriatric Use

Geriatric subjects may be particularly prone to experiencing drowsiness, ataxia and confusion while receiving chlordiazepoxide hydrochloride and clidinium bromide capsules. These effects can usually be avoided with proper dosage adjustment, although they have occasionally been observed even at the lower dosage ranges. Dosing in geriatric subjects should be initiated cautiously (no more than 2 capsules per day) and increased gradually if needed and tolerated (see DOSAGE AND ADMINISTRATION).Chlordiazepoxide hydrochloride and clidinium bromide capsules are contraindicated in the presence of glaucoma, prostatic hypertrophy and benign bladder neck obstruction (see CONTRAINDICATIONS).

ADVERSE REACTIONS

No side effects or manifestation not seen with either compound alone have been reported with the administration of chlordiazepoxide hydrochloride and clidinium bromide capsules. However, since the chlordiazepoxide hydrochloride and clidinium bromide capsules contain chlordiazepoxide hydrochloride and clidinium bromide, the possibility of untoward effects which may be seen with either of these two compounds cannot be excluded.

When chlordiazepoxide hydrochloride has been used alone the necessity of discontinuing therapy because of undesirable effects has been rare. Drowsiness, ataxia and confusion have been reported in some patients – particularly the elderly and debilitated. While these effects can be avoided in almost all instances by proper dosage adjustment, they have occasionally been observed at the lower dosage ranges. In a few instances syncope has been reported.

Other adverse reactions reported during therapy with chlordiazepoxide hydrochloride include isolated instances of skin eruptions, edema, minor menstrual irregularities, nausea and constipation, extrapyramidal symptoms, as well as increased and decreased libido. Such side effects have been infrequent and are generally controlled with reduction of dosage. Changes in EEG patterns (low-voltage fast activity) have been observed in patients during and after chlordiazepoxide hydrochloride treatment.

Blood dyscrasias, including agranulocytosis, jaundice and hepatic dysfunction have occasionally been reported during therapy with chlordiazepoxide hydrochloride. When chlordiazepoxide hydrochloride treatment is protracted, periodic blood counts and liver function tests are advisable.

Adverse effects reported with use of chlordiazepoxide hydrochloride and clidinium bromide capsules are those typical of anticholinergic agents, i.e., dryness of the mouth, blurring of vision, urinary hesitancy and constipation. Constipation has occurred most often when Chlordiazepoxide Hydrochloride/Clidinium Bromide therapy has been combined with other spasmolytic agents and/or low residue diet.

To report SUSPECTED ADVERSE REACTIONS, contact Chartwell RX, LLC at 1-845-232-1683 or FDA at 1-800-FDA-1088 or www.fda.gov/medwatch.

DRUG ABUSE AND DEPENDENCE

Withdrawal symptoms, similar in character to those noted with barbiturates and alcohol (convulsions, tremor, abdominal and muscle cramps, vomiting and sweating), have occurred following abrupt discontinuance of chlordiazepoxide. The more severe withdrawal symptoms have usually been limited to those patients who had received excessive doses over an extended period of time. Generally milder withdrawal symptoms (e.g., dysphoria and insomnia) have been reported following abrupt discontinuance of benzodiazepines taken continuously at therapeutic levels for several months. Consequently, after extended therapy, abrupt discontinuation should generally be avoided and a gradual dosage tapering schedule followed. Addiction-prone individuals (such as drug addicts or alcoholics) should be under careful surveillance when receiving chlordiazepoxide or other psychotropic agents because of the predisposition of such patients to habituation and dependence.

DOSAGE AND ADMINISTRATION

Because of the varied individual responses to tranquilizers and anticholinergics, the optimum dosage of chlordiazepoxide hydrochloride and clidinium bromide capsules varies with the diagnosis and response of the individual patient. The dosage, therefore, should be individualized for maximum beneficial effects. The usual maintenance dose is 1 or 2 capsules, 3 or 4 times a day administered before meals and at bedtime.

Geriatric Dosing

Dosage should be limited to the smallest effective amount to preclude the development of ataxia, oversedation or confusion. The initial dose should not exceed 2 chlordiazepoxide hydrochloride and clidinium bromide capsules per day, to be increased gradually as needed and tolerated.

HOW SUPPLIED

Chlordiazepoxide hydrochloride and clidinium bromide capsules USP, 5 mg/2.5 mg are available in green opaque hard gelatin capsules, each containing 5 mg chlordiazepoxide hydrochloride and 2.5 mg clidinium bromide — bottles of 120 (NDC 62135-696-12) with imprinted "696" on the cap and body of the capsule in black ink.

Store at 20° to 25°C (68° to 77°F); excursions permitted to 15° to 30°C (59° to 86°F) [See USP Controlled Room Temperature].

Keep out of reach of children. Dispense in tight, light-resistant container as defined in USP/NF.

Manufactured for:
Chartwell RX, LLC
Congers, NY 10920

Revised: 04/2022

L70906

MEDICATION GUIDE

Chlordiazepoxide Hydrochloride and Clidinium Bromide Capsules

(klor dye az e pox' ide) (kli di' nee um)

- What is the most important information I should know about chlordiazepoxide hydrochloride and clidinium bromide capsules?Do not stop taking chlordiazepoxide hydrochloride and clidinium bromide capsules without first talking to your healthcare provider. Stopping chlordiazepoxide hydrochloride and clidinium bromide capsules suddenly can cause serious side effects.
- Taking chlordiazepoxide hydrochloride and clidinium bromide capsules with opioid medicines, alcohol, or other central nervous system depressants (including street drugs) can cause severe drowsiness, breathing problems (respiratory depression), coma and death.
- Do not drive, operate heavy machinery, or do other dangerous activities until you know how chlordiazepoxide hydrochloride and clidinium bromide capsules affects you.
- Do not drink alcohol or take other drugs that may make you sleepy or dizzy while taking chlordiazepoxide hydrochloride and clidinium bromide capsules without first talking to your healthcare provider. When taken with alcohol or drugs that cause sleepiness or dizziness, chlordiazepoxide hydrochloride and clidinium bromide capsules may make your sleepiness or dizziness much worse.
- chlordiazepoxide hydrochloride and clidinium bromide capsules can cause abuse and dependence.
- Do not stop taking chlordiazepoxide hydrochloride and clidinium bromide capsules all of a sudden. Stopping chlordiazepoxide hydrochloride and clidinium bromide capsules suddenly can cause seizures, shaking, stomach and muscle cramps, vomiting and sweating.
- Physical dependence is not the same as drug addiction. Your healthcare provider can tell you more about

What are chlordiazepoxide hydrochloride and clidinium bromide capsules?

- Chlordiazepoxide hydrochloride and clidinium bromide capsules are a prescription medicine that are used with other therapies for the treatment of:
- stomach (peptic) ulcers
- irritable bowel syndrome (IBS)
- inflammation of the colon called acute enterocolitis
- chlordiazepoxide hydrochloride and clidinium bromide capsules contains the medicines chlordiazepoxide HCl and clidinium bromide.
- chlordiazepoxide hydrochloride and clidinium bromide capsules can be abused or lead to dependence. Keep chlordiazepoxide hydrochloride and clidinium bromide capsules in a safe place to prevent misuse and abuse. Selling or giving away chlordiazepoxide hydrochloride and clidinium bromide capsules may harm others. Tell your healthcare provider if you have abused or been dependent on alcohol, prescription medicines or street drugs.
- It is not known if chlordiazepoxide hydrochloride and clidinium bromide capsules are safe and effective in children.

Do not take chlordiazepoxide hydrochloride and clidinium bromide capsules if you:

- have glaucoma
- have an enlarged prostate
- have a blockage of your bladder that causes problems with urination
- are allergic to chlordiazepoxide hydrochloride or clidinium bromide

Before you take chlordiazepoxide hydrochloride and clidinium bromide capsules, tell your healthcare provider about all of your medical conditions, including if you:

- have eye problems
- have problems urinating or emptying your bladder
- have coordination problems
- have kidney or liver problems
- have a history of depression, mental illness, or suicidal thoughts
- have a history of drug or alcohol abuse or addiction
- have bleeding problems
- are pregnant or plan to become pregnant. Chlordiazepoxide hydrochloride and clidinium bromide capsules may harm your unborn baby. Avoid taking chlordiazepoxide hydrochloride and clidinium bromide capsules during the first trimester of pregnancy. Tell your healthcare provider right away if you become pregnant during treatment with chlordiazepoxide hydrochloride and clidinium bromide capsules
- are breastfeeding or plan to breastfeed. Chlordiazepoxide hydrochloride and clidinium bromide capsules may pass through your breast milk and may harm your baby. Talk to your healthcare provider about the best way to feed your baby if you take chlordiazepoxide hydrochloride and clidinium bromide capsules. Chlordiazepoxide hydrochloride and clidinium bromide capsules may decrease the amount of breast milk your body makes.

Tell your healthcare provider about all the medicines you take, including prescription and over-the-counter medicines, vitamins, and herbal supplements.

Taking chlordiazepoxide hydrochloride and clidinium bromide capsules with certain other medicines can cause side effects or affect how well chlordiazepoxide hydrochloride and clidinium bromide capsules or the other medicines work.

Do not start or stop other medicines without talking to your healthcare provider.

Especially tell your healthcare provider if you:

- take a monoamine oxidase inhibitor (MAOI) medicine or an anti-psychotic medicine called phenothiazine.

How should I take chlordiazepoxide hydrochloride and clidinium bromide capsules?

- Take chlordiazepoxide hydrochloride and clidinium bromide capsules exactly as your healthcare provider tells you to take it.
- Your healthcare provider may change your dose of chlordiazepoxide hydrochloride and clidinium bromide capsules if needed. Do not change your dose of chlordiazepoxide hydrochloride and clidinium bromide capsules or suddenly stop taking chlordiazepoxide hydrochloride and clidinium bromide capsules without talking with your healthcare provider.
- If you take too much chlordiazepoxide hydrochloride and clidinium bromide capsules, call your healthcare provider or go to the nearest hospital emergency room right away.

What are the possible side effects of chlordiazepoxide hydrochloride and clidinium bromide capsules?

Chlordiazepoxide hydrochloride and clidinium bromide capsules may cause serious side effects, including: See “What is the most important information I should know about chlordiazepoxide hydrochloride and clidinium bromide capsules?”

The most common side effects of chlordiazepoxide hydrochloride and clidinium bromide capsules include:

- dry mouth
- blurred vision
- nausea
- constipation
- skin problems
- swelling
- irregular menstrual (periods) cycles
- increased and decreased desire for sex (libido)
- problems starting to urinate
- drowsiness, coordination problems, and confusion may happen, especially in people who are elderly or weak

These are not all the possible side effects of chlordiazepoxide hydrochloride and clidinium bromide capsules

Call your doctor for medical advice about side effects. You may report side effects to FDA at 1-800-FDA-1088.

How should I store chlordiazepoxide hydrochloride and clidinium bromide capsules?

- Store chlordiazepoxide hydrochloride and clidinium bromide capsules at room temperature 77°F (25°C).
- Keep chlordiazepoxide hydrochloride and clidinium bromide capsules and all medicines out of the reach of children.

General information about the safe and effective use of chlordiazepoxide hydrochloride and clidinium bromide capsules.

Medicines are sometimes prescribed for purposes other than those listed in a Medication Guide. Do not use chlordiazepoxide hydrochloride and clidinium bromide capsules for a condition for which it was not prescribed. Do not give chlordiazepoxide hydrochloride and clidinium bromide capsules to other people, even if they have the same symptoms that you have. It may harm them. You can ask your pharmacist or healthcare provider for information about chlordiazepoxide hydrochloride and clidinium bromide capsules that is written for health professionals.

What are the ingredients in chlordiazepoxide hydrochloride and clidinium bromide capsules?

Active ingredient: chlordiazepoxide hydrochloride and clidinium bromide

Inactive ingredients: corn starch, lactose monohydrate, and talc. Gelatin capsule shells may contain titanium dioxide and sodium lauryl sulfate with the following dye systems: D&C Yellow No. 10, FD&C Green No. 3. The imprinting ink contains ammonia solution, black iron oxide, potassium hydroxide, propylene glycol, and shellac.

Manufactured for:

Chartwell RX, LLC

Congers, NY 10920

USA

For more information, contact Chartwell RX, LLC at 1-845-232-1683.

This Medication Guide has been approved by the U.S. Food and Drug Administration.

Revised: 05/2022

L70907

PACKAGE LABEL,PRINICIPAL DISPLAY PANEL

Chlordiazepoxide HCL and Clidinium Bromide Capsules,USP- NDC-62135-696 - 12 - 120's Bottle Label